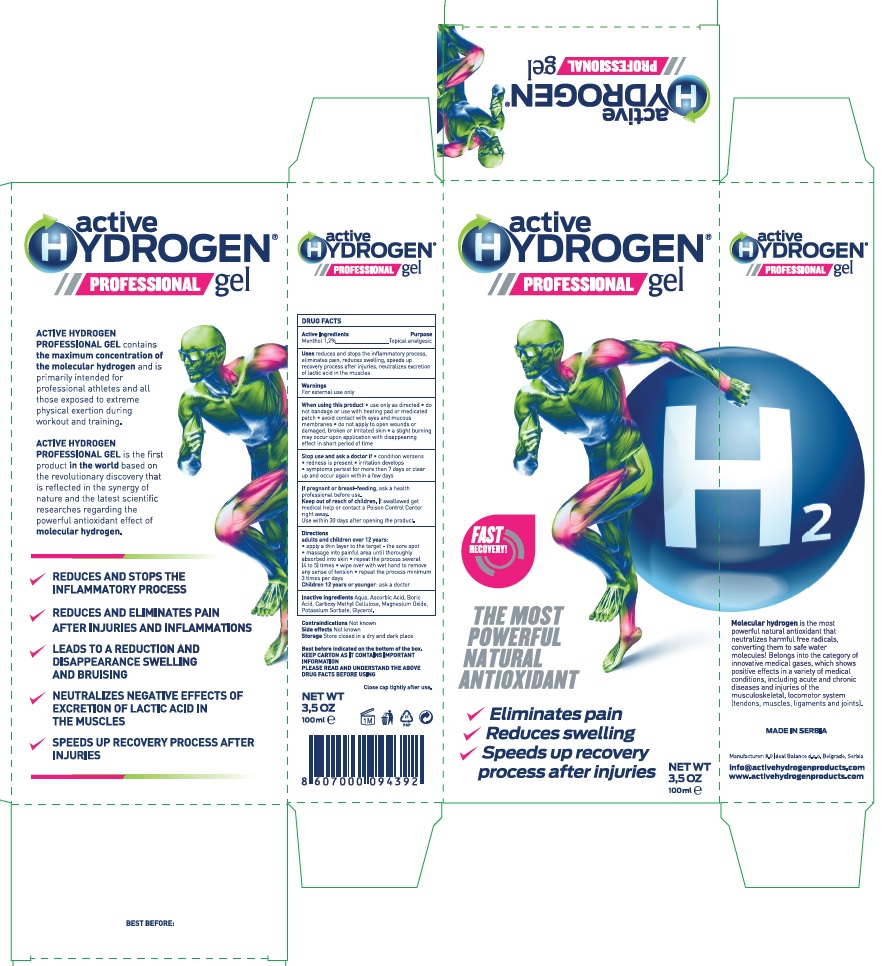 DRUG LABEL: Active HYDROGEN Professional gel
NDC: 72901-001 | Form: GEL
Manufacturer: 8.0 IDEAL BALANCE D.O.O. BEOGRAD
Category: otc | Type: HUMAN OTC DRUG LABEL
Date: 20190313

ACTIVE INGREDIENTS: MENTHOL 12 mg/1 mL
INACTIVE INGREDIENTS: AQUA REGIA; ASCORBIC ACID; BORIC ACID; CARBOXYMETHYLCELLULOSE; MAGNESIUM OXIDE; POTASSIUM SORBATE; GLYCEROL (1-(12-HYDROXYSTEARATE))

active HYDROGEN Professional gel

Warnings

- For external use only
- When using this product

• use only as directed

• do not bandage or use with heating pad or medicated patch

• avoid contact with eyes and mucous membranes

• do not apply to open wounds or damaged, broken or irritated skin

• a slight burning may occur upon application with disappearing effect in short period of time

Purpose

Topical analgesic

Uses

Reduces and stops the inflammatory process, eliminates pain, reduces swelling, speeds up
recovery process after injuries, neutralizes excretion of lactic acid in the muscles

Dosage and Administration

adults and children over 12 years:
• apply a thin layer to the target - the sore spot
• massage into painful area until thoroughly absorbed into skin

• repeat the process several (4 to 5) times • wipe over with wet hand to remove any sense of tension

• repeat the process minimum 3 times per days Children 12 years or younger: ask a doctor

KEEP OUT OF REACH OF CHILDREN

If preganant or breast-feeding, ask a health professional before use.

Keep out of reach of children

If swallowed get medical help or contact a Poison Control Center right away

Stop use and ask doctor if

• condition worsens

• redness is present

• irritation develops
• symptoms persist for more then 7 days or clear up and occur again within a few days

Active ingredient

Menthol 1.2 %

Inactive Ingredients

Aqua, Ascorbic Acid, Boric Acid, Carboxy Methyl Cellulose, Magnesium Oxide, Potassium Sorbate, Glycerol.